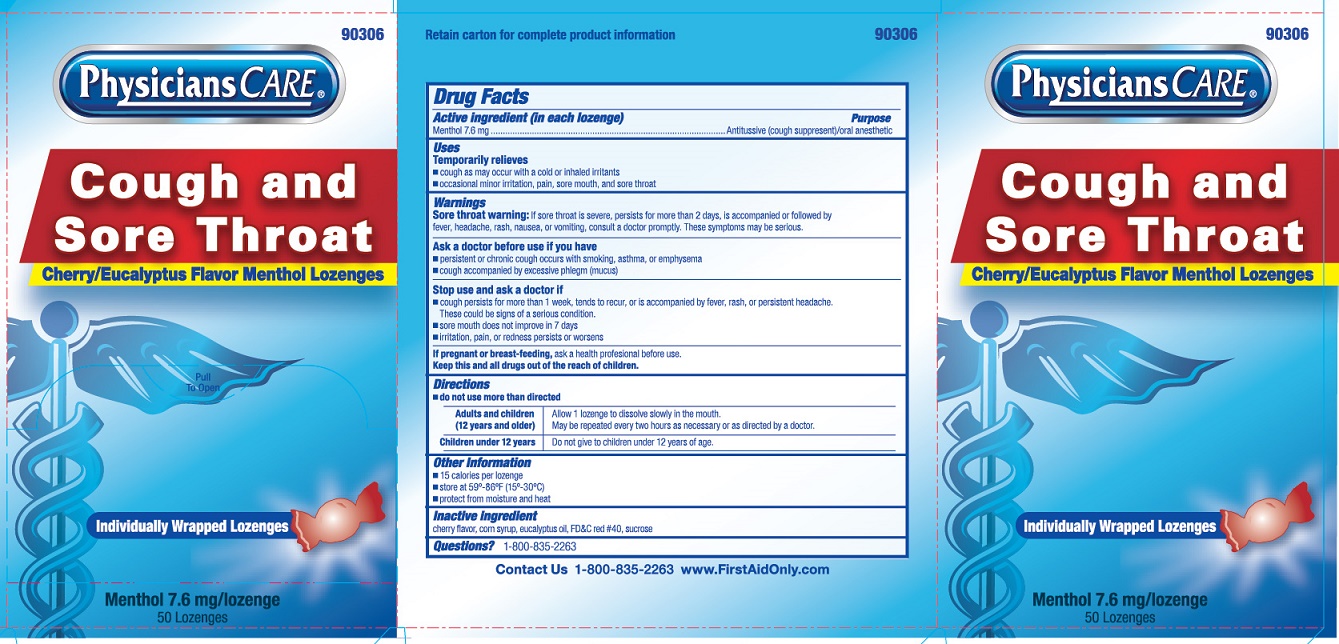 DRUG LABEL: Physicians Care Cough and Sore Throat
NDC: 0924-0150 | Form: LOZENGE
Manufacturer: Acme United Corporation
Category: otc | Type: HUMAN OTC DRUG LABEL
Date: 20250908

ACTIVE INGREDIENTS: MENTHOL 7.6 mg/1 1
INACTIVE INGREDIENTS: EUCALYPTUS OIL; HIGH FRUCTOSE CORN SYRUP; SUCROSE; FD&C RED NO. 40

Physicians Care Cough and Sore Throat

Drug Facts

Active ingredient (in each lozenge)

Menthol 7.6 mg

Purpose

Antitussive (cough suppressant)/oral anesthetic

Uses

Temporarily relieves

■ cough as may occur with a cold or inhaled irritants

■ occasional minor irritation and sore throat

Warnings

Sore throat warning: If sore throat is severe, persists for more than 2 days, is accompanied or followed by fever, headache, rash, nausea, or vomiting, consult a doctor promptly. These symptoms may be serious.

Ask a doctor before use if you have

■ persistent or chronic cough occurs with smoking, asthma, or emphysema

■ cough accompanied by excessive phlegm (mucus)

Stop use and ask a doctor if

■ cough persists for more than 1 week, tends to recur, or is accompanied by fever, rash, or persistent
headache. These could be signs of a serious condition.

■ sore mouth does not improve in 7 days

■ irritation, pain, or redness persists or worsens

If pregnant or breast feeding,

ask a health professional before use.

Directions

■ do not use more than directed

Adults and children: (12 years and older)

Allow 1 lozenge to dissolve slowly in the mouth. May be repeated every 2 hours as necessary or as directed by a doctor.

Children under 12 years:

Do not give to children under 12 years of age.

Other information

■ 15 calories per lozenge

■ store at 59º-86ºF (15º-30ºC)

■ protect from moisture & heat

Inactive ingredients

cherry flavor, corn syrup, eucalyptus oil, FD&C red #40, sucrose

Questions?

1-800-835-2263

Physicians Care Cough and Sore Throat Label

90306

Physicians Care®

Cough and Sore Throat

Cherry/Eucalyptus Flavor Menthol Lozenges

Pull To Open

Individually Wrapped Lozenges

Menthol 7.6 mg/lozenge

50 Lozenges